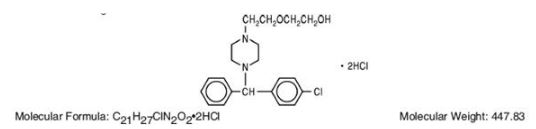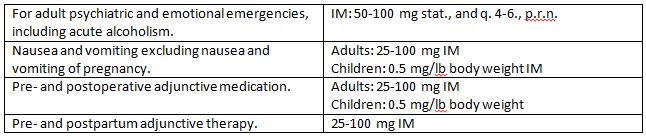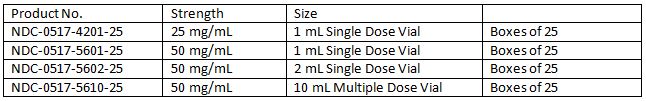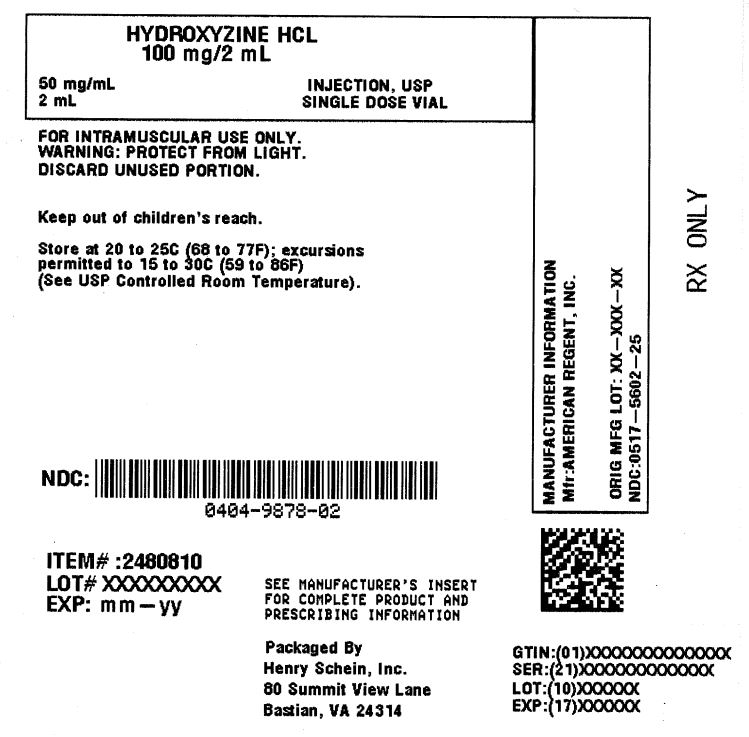 DRUG LABEL: Hydroxyzine
NDC: 0404-9878 | Form: INJECTION, SOLUTION
Manufacturer: Henry Schein, Inc.
Category: prescription | Type: HUMAN PRESCRIPTION DRUG LABEL
Date: 20251031

ACTIVE INGREDIENTS: HYDROXYZINE DIHYDROCHLORIDE 50 mg/1 mL
INACTIVE INGREDIENTS: HYDROCHLORIC ACID; SODIUM HYDROXIDE

Hydroxyzine HCL 50mg/mL Injection, USP 2 mL Single Dose Vial

Description

Hydroxyzine hydrochloride has the chemical name of (±)-2-[2-[4-(p-Chloro-a phenylbenzyl) -1-piperazinyl]ethoxy]ethanol dihydrochloride and occurs as a white, odorless powder which is very soluble in water.

It has the following structural formula:

Hydroxyzine Hydrochloride Injection, USP is a sterile aqueous solution intended for intramuscular administration.

Each mL contains: Hydroxyzine HCI 25 mg or 50 mg, Benzyl Alcohol 0.9%, and Water for Injection q.s. pH adjusted with Sodium Hydroxide and/or Hydrochloric Acid.

Clinical Pharmacology

Hydroxyzine hydrochloride is unrelated chemically to phenothiazine, reserpine, and meprobamate. Hydroxyzine has demonstrated its clinical effectiveness in the chemotherapeutic aspect of the total management of neuroses and emotional disturbances manifested by anxiety, tension, agitation, apprehension or confusion.

Hydroxyzine has been shown clinically to be a rapid-acting true ataraxic with a wide margin of safety. It induces a calming effect in anxious, tense, psychoneurotic adults and also in anxious, hyperkinetic children without impairing mental alertness. It is not a cortical depressant, but its action may be due to a suppression of activity in certain key regions of the subcortical area of the central nervous system.

Primary skeletal muscle relaxation has been demonstrated experimentally.

Hydroxyzine has been shown experimentally to have antispasmodic properties, apparently mediated through interference with the mechanism that responds to spasmogenic agents such as serotonin, acetylcholine, and histamine.

Antihistaminic effects have been demonstrated experimentally and confirmed clinically.

An antiemetic effect, both by the apomorphine test and the veriloid test, has been demonstrated. Pharmacological and clinical studies indicate that hydroxyzine in therapeutic dosage does not increase gastric secretion or acidity and in most cases provides mild antisecretory benefits.

Indications and Usage

The total management of anxiety, tension, and psychomotor agitation in conditions of emotional stress requires in most instances a combined approach of psychotherapy and chemotherapy. Hydroxyzine has been found to be particularly useful for this latter phase of therapy in its ability to render the disturbed patient more amenable to psychotherapy in long term treatment of the psychoneurotic and psychotic, although it should not be used as the sole treatment of psychosis or of clearly demonstrated cases of depression.

Hydroxyzine is also useful in alleviating the manifestations of anxiety and tension as in the preparation for dental procedures and in acute emotional problems. It has also been recommended for the management of anxiety associated with organic disturbances and as adjunctive therapy in alcoholism and allergic conditions with strong emotional overlay, such as in asthma, chronic urticaria, and pruritus.

Hydroxyzine hydrochloride intramuscular solution is useful in treating the following types of patients when intramuscular administration is indicated:

1. The acutely disturbed or hysterical patient.

2. The acute or chronic alcoholic with anxiety withdrawal symptoms or delirium tremens.

3. As pre- and postoperative and pre- and postpartum adjunctive medication to permit reduction in narcotic dosage, allay anxiety and control emesis.

Hydroxyzine hydrochloride has also demonstrated effectiveness in controlling nausea and vomiting, excluding nausea and vomiting of pregnancy. (See CONTRAINDICATIONS).

In prepartum states, the reduction in narcotic requirement effected by hydroxyzine is of particular benefit to both mother and neonate.

Hydroxyzine benefits the cardiac patient by its ability to allay the associated anxiety and apprehension attendant to certain types of heart disease. Hydroxyzine is not known to interfere with the action of digitalis in any way and may be used concurrently with this agent.

The effectiveness of hydroxyzine in long term use, that is, more than 4 months, has not been assessed by systematic clinical studies. The physician should reassess periodically the usefulness of the drug for the individual patient.

Contraindications

Hydroxyzine hydrochloride intramuscular solution is intended only for intramuscular administration and should not, under any circumstances, be injected subcutaneously, intra arterially or intravenously.

Hydroxyzine is contraindicated in patients with a prolonged QT interval.

This drug is contraindicated for patients who have shown a previous hypersensitivity to it.

Hydroxyzine, when administered to the pregnant mouse, rat, and rabbit, induced fetal abnormalities in the rat at doses substantially above the human therapeutic range. Clinical data in human beings are inadequate to establish safety in early pregnancy. Until such data are available, hydroxyzine is contraindicated in early pregnancy.

Warnings

Tissue damage: Intramuscular hydroxyzine hydrochloride may result in severe injection site reactions (including extensive tissue damage, necrosis and gangrene) requiring surgical intervention (including debridement, skin grafting and amputation).

PRECAUTIONS

THE POTENTIATING ACTION OF HYDROXYZINE MUST BE CONSIDERED WHEN THE DRUG IS USED IN CONJUNCTION WITH CENTRAL NERVOUS SYSTEM DEPRESSANTS SUCH AS NARCOTICS, BARBITURATES AND ALCOHOL. Rarely, cardiac arrests and death have been reported in association with the combined use of hydroxyzine hydrochloride intramuscularly and other CNS depressants. Therefore, when central nervous system depressants are administered concomitantly with hydroxyzine their dosage should be reduced up to 50 percent. The efficacy of hydroxyzine as adjunctive pre- and postoperative sedative medication has also been well established, especially as regards its ability to allay anxiety, control emesis, and reduce the amount of narcotic required.

HYDROXYZINE MAY POTENTIATE NARCOTICS AND BARBITURATES, so their use in preanesthetic adjunctive therapy should be modified on an individual basis. Atropine and other belladonna alkaloids are not affected by the drug.

When hydroxyzine is used preoperatively or prepartum, narcotic requirements may be reduced as much as 50 percent. Thus, when 50 mg of hydroxyzine hydrochloride intramuscular solution is employed, meperidine dosage may be reduced from 100 mg to 50 mg. The administration of meperidine may result in severe hypotension in the postoperative patient or any individual whose ability to maintain blood pressure has been compromised by a depleted blood volume. Meperidine should be used with great caution and in reduced dosage in patients who are receiving other pre- and/or postoperative medications and in whom there is a risk of respiratory depression, hypotension, and profound sedation or coma occurring. Before using any medications concomitant with hydroxyzine, the manufacturer"s prescribing information should be read carefully.

Since drowsiness may occur with the use of this drug, patients should be warned of this possibility and cautioned against driving a car or operating dangerous machinery while taking this drug.

As with all intramuscular preparations, hydroxyzine hydrochloride intramuscular solution should be injected well within the body of a relatively large muscle. Inadvertent subcutaneous injection may result in significant tissue damage.

Adults
The preferred site is the upper outer quadrant of the buttock, (i.e., the gluteus maximus), or the mid-lateral thigh.

Children
It is recommended that intramuscular injections be given preferably in the mid-lateral muscles of the thigh. In infants and small children the periphery of the upper outer quadrant of the gluteal region should be used only when necessary, such as in burn patients, in order to minimize the possibility of damage to the sciatic nerve.

The deltoid area should be used only if well developed such as in certain adults and older children, and then only with caution to avoid radial nerve injury. Intramuscular injections should not be made into the lower and mid-third of the upper arm. As with all intramuscular injections, aspiration is necessary to help avoid inadvertent injection into a blood vessel.

Geriatric Use
A determination has not been made whether controlled clinical studies of hydroxyzine hydrochloride included sufficient numbers of subjects aged 65 and over to define a difference in response from younger subjects. Other reported clinical experience has not identified differences in responses between the elderly and younger patients. In general, dose selection for an elderly patient should be cautious, usually starting at the low end of the dosing range, reflecting the greater frequency of decreased hepatic, renal or cardiac function, and of concomitant disease or other drug therapy.

The extent of renal excretion of hydroxyzine hydrochloride has not been determined. Because elderly patients are more likely to have decreased renal function, care should be taken in dose selections.

Sedating drugs may cause confusion and over-sedation in the elderly; elderly patients generally should be started on low doses of hydroxyzine hydrochloride and observed closely.

CASES OF QT PROLONGATION AND TORSADE DE POINTES HAVE BEEN REPORTED DURING POST-MARKETING USE OF HYDROXYZINE. The majority of reports occurred in patients with other risk factors for QT prolongation or Torsade de Pointes (pre-existing heart disease, electrolyte imbalances or concomitant arrhythmogenic drug use). Therefore, hydroxyzine should be used with caution in patients with risk factors for QT prolongation, congenital long QT syndrome, a family history of long QT syndrome, other conditions that predispose to QT prolongation and ventricular arrhythmia, as well as recent myocardial infarction, uncompensated heart failure, and bradyarrhythmias.

Caution is recommended during the concomitant use of drugs known to prolong the QT interval. These include Class 1A (e.g., quinidine, procainamide) or Class III (e.g., amiodarone, sotalol) antiarrhythmics, certain antipsychotics (e.g., ziprasidone, iloperidone, clozapine, quetiapine, chlorpromazine), certain antidepressants (e.g., citalopram, fluoxetine), certain antibiotics (e.g., azithromycin, erythromycin, clarithromycin, gatifloxacin, moxifloxacin); and others (e.g., pentamidine, methadone, ondansetron, droperidol).

Acute Generalized Exanthematous Pustulosis (AGEP)
Hydroxyzine may rarely cause acute generalized exanthematous pustulosis (AGEP), a serious skin reaction characterized by fever and numerous small, superficial, nonfollicular, sterile pustules, arising within large areas of edematous erythema. Inform patients about the signs of AGEP, and discontinue hydroxyzine at the first appearance of a skin rash, worsening of pre-existing skin reactions which hydroxyzine may be used to treat, or any other sign of hypersensitivity. If signs or symptoms suggest AGEP, use of hydroxyzine should not be resumed and alternative therapy should be considered. Avoid cetirizine or levocetirizine in patients who have experienced AGEP or other hypersensitivity reactions with hydroxyzine, due to the risk of cross-sensitivity.

Adverse Reactions

Therapeutic doses of hydroxyzine seldom produce impairment of mental alertness. However, drowsiness may occur; if so, it is usually transitory and may disappear in a few days of continued therapy or upon reduction of the dose. Dryness of the mouth may be encountered at higher doses. Extensive clinical use has substantiated the absence of toxic effects on the liver or bone marrow when administered in the recommended doses for over four years of uninterrupted therapy. The absence of adverse effects has been further demonstrated in experimental studies in which excessively high doses were administered.

Involuntary motor activity, including rare instances of tremor and convulsions, has been reported, usually with doses considerably higher than those recommended. Continuous therapy with over one gram per day has been employed in some patients without these effects having been encountered. Hydroxyzine hydrochloride is associated with Acute Generalized Exanthematous Pustulosis (AGEP) in post marketing reports.

Dosage And Administration

The recommended dosages for hydroxyzine hydrochloride intramuscular solution are:

As with all potent medications, the dosage should be adjusted according to the patient's response to therapy.

FOR ADDITIONAL INFORMATION ON THE ADMINISTRATION AND SITE OF SELECTION SEE PRECAUTIONS SECTION. NOTE: Hydroxyzine hydrochloride intramuscular solution may be administered without further dilution.

Patients may be started on intramuscular therapy when indicated. They should be maintained on oral therapy whenever this route is practicable.

Parenteral drug products should be inspected visually for particulate matter and discoloration prior to administration, whenever solution and container permit.

How Supplied

Storage Condition: Store at 20° to 25°C (68° to 7JOF); excursions permitted to 15° to 30°C (59° to 86°F) (See USP Controlled Room Temperature). Protect from light. Discard unused portion of the single dose vial.

Product repackaged by: Henry Schein, Inc., Bastian, VA 24314
From Original Manufacturer/Distributor's NDC and Unit of Sale | To Henry Schein Repackaged Product NDC and Unit of Sale | Total Strength/Total Volume (Concentration) per unit
NDC 0517-5601-25 Boxes of 25 | NDC 0404-9877-01 1 1mL Single Dose Vial in a bag (Vial bears NDC 0517-5601-25) | 50 mg/mL
NDC 0517-5602-25 Boxes of 25 | NDC 0404-9878-02 1 2 mL Single Dose Vial in a bag (Vial bears NDC 0517-5602-25) | 50 mg/mL

AMERICAN REGENT, INC.

SHIRLEY, NY 11967

IN4201

Rev. 10/16

MG #7842